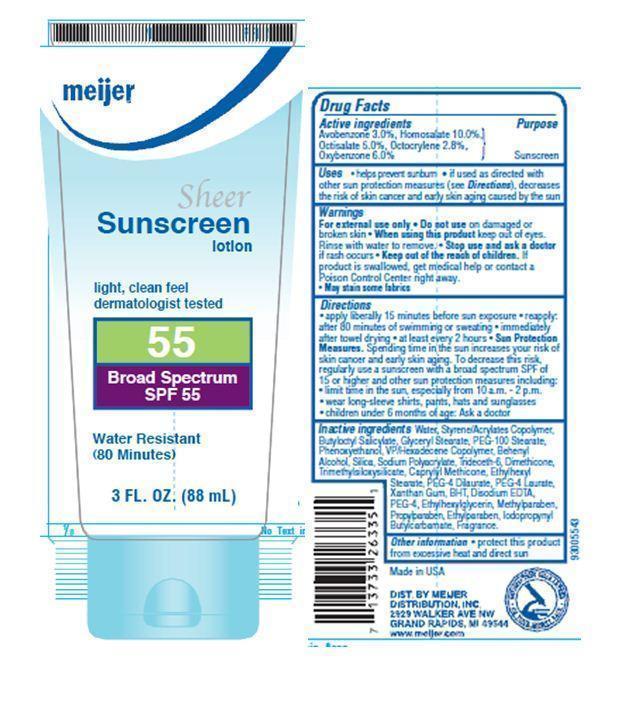 DRUG LABEL: Meijer Sheer SPF 55
NDC: 41250-019 | Form: LOTION
Manufacturer: Meijer Distribution Inc
Category: otc | Type: HUMAN OTC DRUG LABEL
Date: 20120101

ACTIVE INGREDIENTS: AVOBENZONE 3 mL/100 mL; HOMOSALATE 10 mL/100 mL; OCTISALATE 5 mL/100 mL; OCTOCRYLENE 2.8 mL/100 mL; OXYBENZONE 6 mL/100 mL
INACTIVE INGREDIENTS: WATER; BUTYLOCTYL SALICYLATE; GLYCERYL MONOSTEARATE; PEG-100 STEARATE; PHENOXYETHANOL; DOCOSANOL; SILICON DIOXIDE; SODIUM POLYACRYLATE (2500000 MW); TRIDECETH-6; DIMETHICONE; ETHYLHEXYL STEARATE; PEG-4 DILAURATE; PEG-4 LAURATE; XANTHAN GUM; BUTYLATED HYDROXYTOLUENE; EDETATE DISODIUM; POLYETHYLENE GLYCOL 200; ETHYLHEXYLGLYCERIN; METHYLPARABEN; PROPYLPARABEN; ETHYLPARABEN; IODOPROPYNYL BUTYLCARBAMATE

Drug Facts

Active Ingredients

Avobenzone 3.0%
Homosalate 10.0%
Octisalate 5.0%
Octocrylene 2.8%
Oxybenzone 6.0%

Purpose

Sunscreen

Uses

Helps prevent sunburn. If used as directed, with other sun protection measures (see Directions), decreases the risk of skin cancer and early skin aging caused by the sun.

Warnings

For external use only. Do not use on damaged or broken skin.

When using this product

Keep out of eyes. Rinse with water to remove.

Stop use and ask a doctor

if rash occurs

Keep out of reach of children

If swallowed, get medical help or contact a Poison Control Center right away. May stain some fabrics.

Directions

- apply liberally 15 minutes before sun exposure
- reapply
- after 80 minutes of swimming or sweating
- immediately after towel drying
- at least every 2 hours
- Sun Protection Measures: Spending time in the sun increases your risk of skin cancer and early skin aging. To decrease this risk, regularly use a sunscreen with a broad spectrum SPF of 15 or higher and other sun protection measures including:
- limit time in the sun, especially from 10 a.m. - 2 p.m.
- wear long-sleeve shirts, pants, hats and sunglasses
- children under 6 months of age: Ask a doctor

Inactive ingredients

Water, Styrene/Acrylates Copolymer, Butyloctyl Salicylate, Glyceryl Stearate, PEG-100 Stearate, Phenoxyethanol, VP/Hexadecene Copolymer, Behenyl Alcohol, Silica, Sodium Polyacrylate, Trideceth-6, Dimethicone, Trimethylsiloxysilicate, Caprylyl Methicone, Ethylhexyl Stearate, PEG-4 Dilaurate, PEG-4 Laurate, Xanthan Gum, BHT, Disodium EDTA, PEG-4, Ethylhexylglycerin, Methylparaben, Propylparaben, Ethylparaben, Iodopropynyl Butylcarbamate, Fragrance.

Other Information

protect this product from excessive heat and direct sun